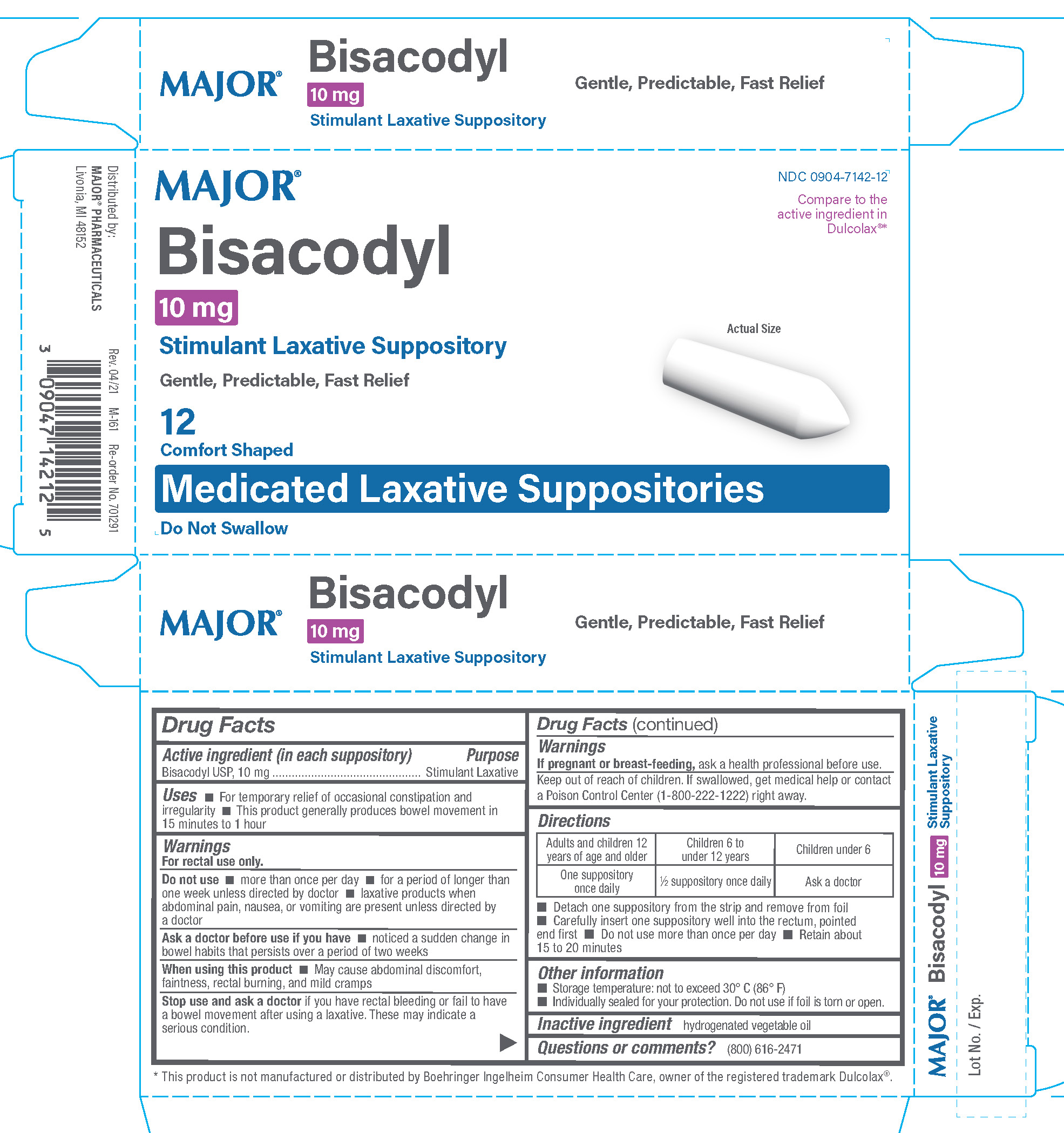 DRUG LABEL: Bisacodyl							
NDC: 0904-7142 | Form: SUPPOSITORY
Manufacturer: Major Pharmaceuticals
Category: otc | Type: HUMAN OTC DRUG LABEL
Date: 20251024

ACTIVE INGREDIENTS: BISACODYL 10 mg/1 1
INACTIVE INGREDIENTS: HYDROGENATED PALM KERNEL OIL

Major Bisacodyl Suppositories

Active ingredient (in each suppository)

Bisacodyl USP, 10mg

Purpose

Stimulant Laxative

Uses

- for temporary relief of occasional constipation and irregularity
- this product generally produces bowel movement in 15 minutes to 1 hour

Warnings

For rectal use only

Do not use

- more than once per day
- for a period longer than one week unless directed by a doctor
- laxative products when abdominal pain, nausia, or vomiting are present unless directed a doctor

Ask a Doctor before using any laxative if you have

- notice a sudden change in bowel habits that lasts more than 2 weeks

When using this product

- may cause stomach discomfort, faintness, rectal burning and mild cramps

Stop use and ask a doctor if

you have rectal bleeding or fail to have a bowel movement after using a laxative. These may indicate a serious condition.

If pregnant or breast feeding,

ask a health professional before use.

Keep out of reach of children.

If swallowed, get medical help or contact a Poison Control Center (1-800-222-1222) right away.

Directions

Adults and children 12 years of age and over - One suppository once daily

Children 6 to under 12 years of age - 1/2 suppository once daily

Children under 6 - Ask a doctor

- Detach one suppository from the strip and remove the foil
- Carefully insert one suppository well into the rectum, pointed end first
- Do not use more than once per day
- Retain about 15 to 20 minutes

Other information

- Storage temperature not to exceed 30ºC (86ºF)
- Indiviually sealed for your protection. Do not use if foil is torn or open.

Inactive ingredients

hydrogenated vegetable oil

Questions or comments?

(800) 616-2471

Major Bisacodyl Suppositories

Major_Bisacodyl_12.jpg

The product package shown above represents a sample of that currently in use. Additional packaging may also be available.

Bisacodyl Suppositories 12ct

Distributed by

Major Pharmaceuticals

Livonia, MI 48152